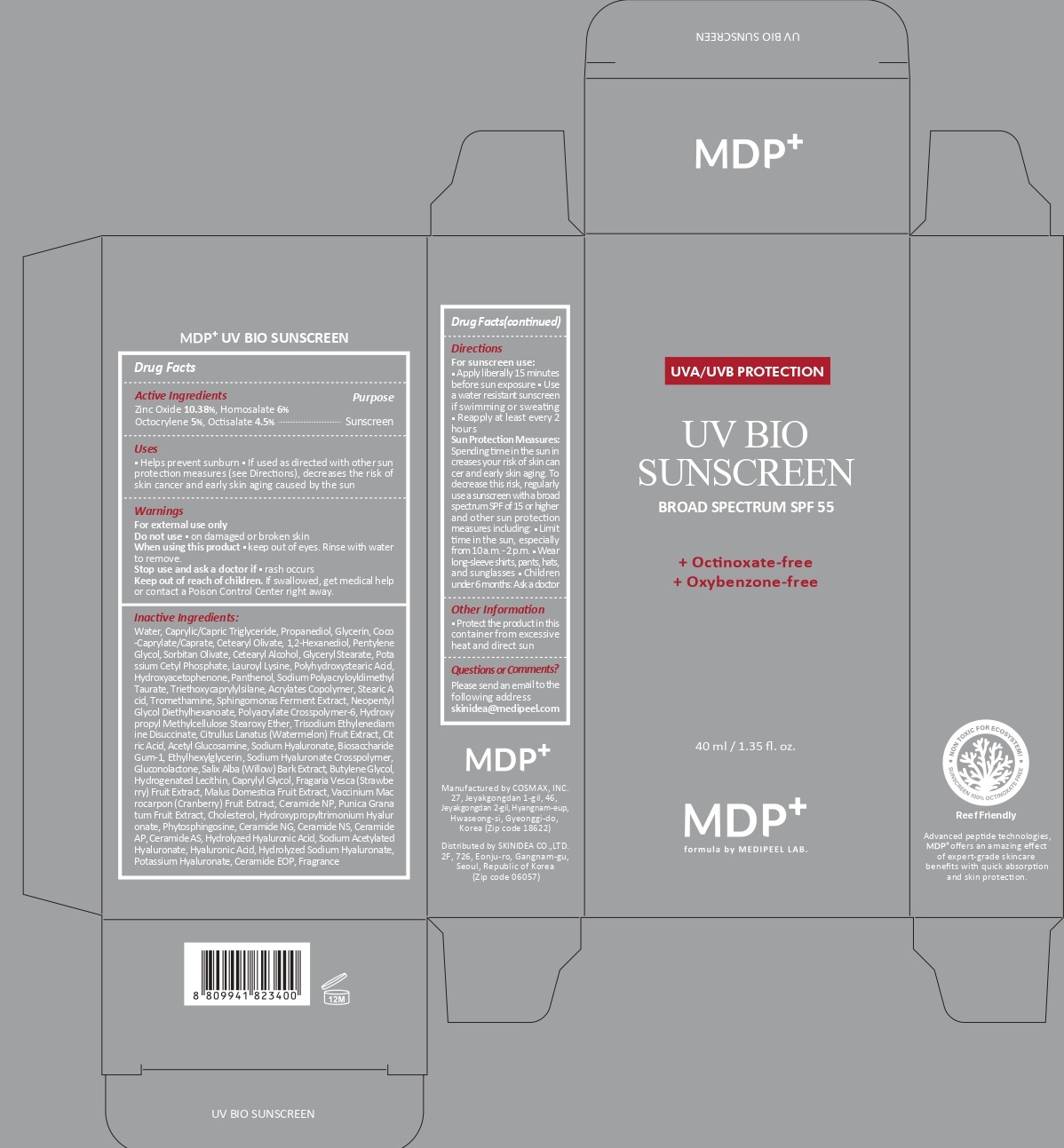 DRUG LABEL: MDP UV BIO SUNSCREEN
NDC: 72220-003 | Form: CREAM
Manufacturer: SKINIDEA CO., LTD
Category: otc | Type: HUMAN OTC DRUG LABEL
Date: 20250317

ACTIVE INGREDIENTS: ZINC OXIDE 103.8 mg/1 mL; HOMOSALATE 60 mg/1 mL; OCTOCRYLENE 50 mg/1 mL; OCTISALATE 45 mg/1 mL
INACTIVE INGREDIENTS: WATER; MEDIUM-CHAIN TRIGLYCERIDES; PROPANEDIOL; GLYCERIN; COCOYL CAPRYLOCAPRATE; CETEARYL OLIVATE; 1,2-HEXANEDIOL; PENTYLENE GLYCOL; SORBITAN OLIVATE; CETOSTEARYL ALCOHOL; GLYCERYL MONOSTEARATE; POTASSIUM CETYL PHOSPHATE; LAUROYL LYSINE; HYDROXYACETOPHENONE; PANTHENOL; SODIUM POLYACRYLOYLDIMETHYL TAURATE; TRIETHOXYCAPRYLYLSILANE; STEARIC ACID; TROMETHAMINE; NEOPENTYL GLYCOL DIETHYLHEXANOATE; AMMONIUM ACRYLOYLDIMETHYLTAURATE, DIMETHYLACRYLAMIDE, LAURYL METHACRYLATE AND LAURETH-4 METHACRYLATE COPOLYMER, TRIMETHYLOLPROPANE TRIACRYLATE CROSSLINKED (45000 MPA.S); TRISODIUM ETHYLENEDIAMINE DISUCCINATE; WATERMELON; CITRIC ACID MONOHYDRATE; N-ACETYLGLUCOSAMINE; HYALURONATE SODIUM; BIOSACCHARIDE GUM-1; ETHYLHEXYLGLYCERIN; GLUCONOLACTONE; SALIX ALBA BARK; BUTYLENE GLYCOL; CAPRYLYL GLYCOL; FRAGARIA VESCA FRUIT; APPLE; CRANBERRY; CERAMIDE NP; POMEGRANATE; CHOLESTEROL; PHYTOSPHINGOSINE; CERAMIDE NG; CERAMIDE NS; CERAMIDE AP; SODIUM ACETYLATED HYALURONATE; HYALURONIC ACID

MDP UV BIO SUNSCREEN

Active Ingredients

Zinc Oxide 10.38%, Homosalate 6%
Octocrylene 5%, Ethylhexyl salicylate 4.5%

Purpose

Sunscreen

Uses

- Helps prevent sunburn
- If used as directed with other sun protection measures (see Directions), decreases the risk of skin cancer and early skin aging caused by the sun

Warnings

■ For external use only.

■ Do not use ● on damaged or broken skin

■ When using this product ● keep out of eyes. Rinse with water to remove.

■ Stop use and ask a doctor if ● rash occurs

■ Keep out of reach of children. If swallowed, get medical help or contact a Poison Control Center right away.

Do not use

- on damaged or broken skin

When using this product

- keep out of eyes. Rinse with water to remove.

Stop use and ask a doctor if

- rash occurs

Keep out of reach of children.

If swallowed, get medical help or contact a Poison Control Center right away.

Directions

For sunscreen use:

■ Apply liberally 15 minutes before sun exposure

■ Use a water-resistant sunscreen if swimming or sweating

■ Reapply at least every 2 hours

■ Sun Protection Measures: Spending time in the sun in creases your risk of

Sun Protection Measures.

Spending time in the sun in creases your risk of skin cancer and early skin aging. To decrease this risk, regularly use a sunscreen with a broad spectrum SPF of 15 or higher and other sun protection measures including: ● Limit time in the sun, especially from 10 a.m.-2 p.m. ● Wear long-sleeve shirts, pants, hats, and sunglasses ● Children under 6 months: Ask a doctor

Inactive ingredients:

Water, Caprylic/Capric Triglyceride, Propanediol, Glycerin, Coco-Caprylate/Caprate, Cetearyl Olivate, 1,2-Hexanediol, Pentylene Glycol, Sorbitan Olivate, Cetearyl Alcohol, Glyceryl Stearate, Potassium Cetyl Phosphate, Lauroyl Lysine, Polyhydroxystearic Acid, Hydroxyacetophenone, Panthenol, Sodium Polyacryloyldimethyl Taurate, Triethoxycaprylylsilane, Acrylates Copolymer, Stearic Acid, Tromethamine, Sphingomonas Ferment Extract, Neopentyl Glycol Diethylhexanoate, Polyacrylate Crosspolymer-6, Hydroxypropyl Methylcellulose Stearoxy Ether, Trisodium Ethylenediamine Disuccinate, Citrullus Lanatus (Watermelon) Fruit Extract, Citric Acid, Acetyl Glucosamine, Sodium Hyaluronate, Biosaccharide Gum-1, Ethylhexylglycerin, Sodium Hyaluronate Crosspolymer, Gluconolactone, Salix Alba (Willow) Bark Extract, Butylene Glycol, Hydrogenated Lecithin, Caprylyl Glycol, Fragaria Vesca (Strawberry) Fruit Extract, Malus Domestica Fruit Extract, Vaccinium Macrocarpon (Cranberry) Fruit Extract, Ceramide NP, Punica Granatum Fruit Extract, Cholesterol, Hydroxypropyltrimonium Hyaluronate, Phytosphingosine, Ceramide NG, Ceramide NS, Ceramide AP, Ceramide AS, Hydrolyzed Hyaluronic Acid, Sodium Acetylated Hyaluronate, Hyaluronic Acid, Hydrolyzed Sodium Hyaluronate, Potassium Hyaluronate, Ceramide EOP, Fragrance

Other information

- Protect the product in this container from excessive heat and direct sun

Questions or comments?

Please send an email to the following address
skinidea@medipeel.com